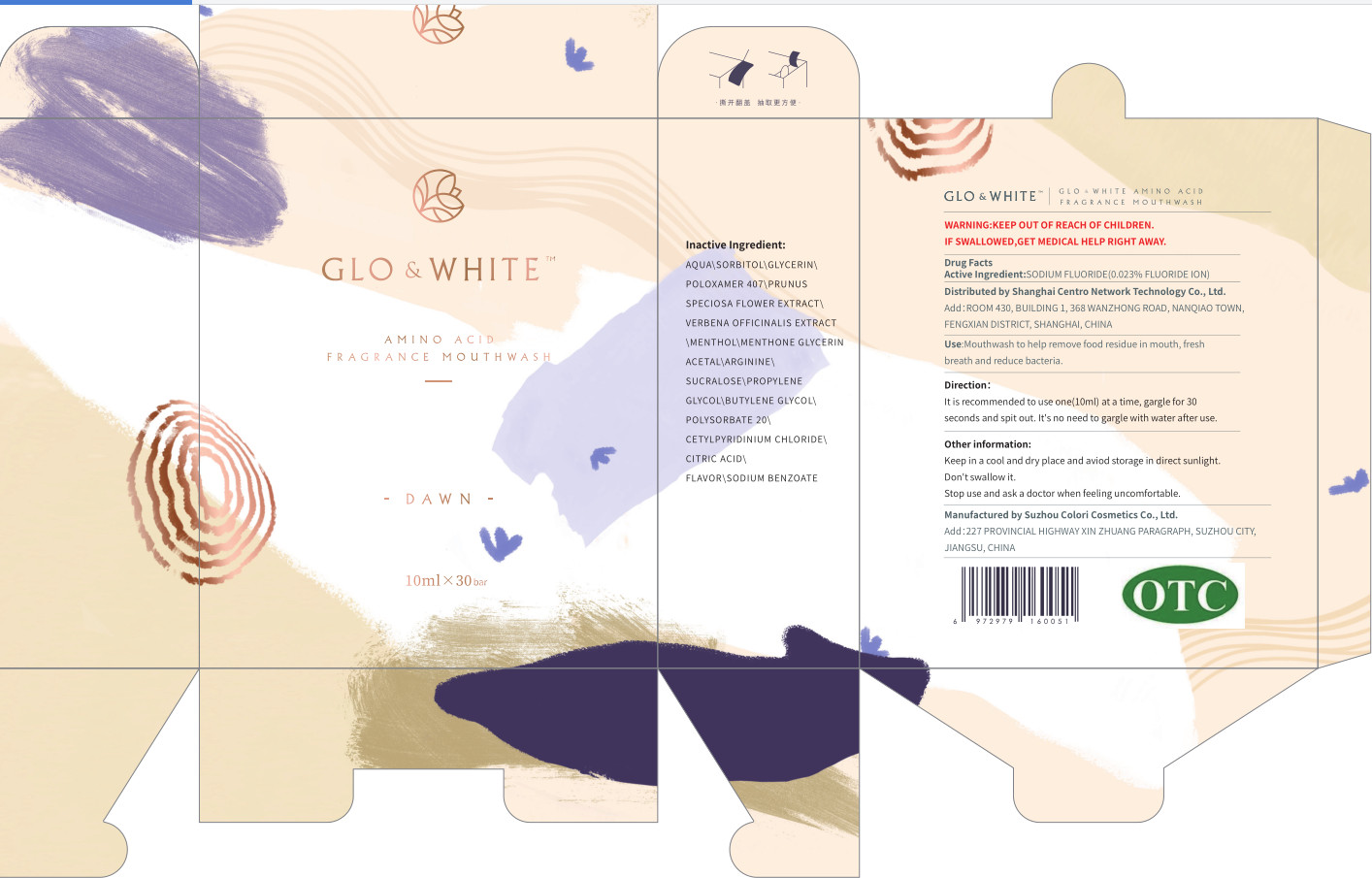 DRUG LABEL: AMINO ACID FRAGRANCEMOUTHWASH DAWN
NDC: 55409-002 | Form: LIQUID
Manufacturer: Shanghai Centro Network Technology Co., Ltd.
Category: otc | Type: HUMAN OTC DRUG LABEL
Date: 20201019

ACTIVE INGREDIENTS: SODIUM FLUORIDE 0.005 g/10 mL
INACTIVE INGREDIENTS: WATER; GLYCERIN; VERBENA OFFICINALIS; ARGININE; PROPYLENE GLYCOL; CETYLPYRIDINIUM CHLORIDE; METHYL SALICYLATE; SORBITOL; POLOXAMER 407; BUTYLENE GLYCOL; SODIUM BENZOATE; PRUNUS SPECIOSA FLOWER; SUCRALOSE; MENTHOL; POLYSORBATE 20; CITRIC ACID MONOHYDRATE; MENTHONE 1,2-GLYCEROL KETAL, (+/-)-

DOSAGE AND ADMINISTRATION

Keep in a cool and dry place and aviod storage in direct sunlight.

INACTIVE INGREDIENT

AQUA、SORBITOL、GLYCERIN、POLOXAMER 407、PRUNUS SPECIOSA FLOWER EXTRACT、VERBENA OFFICINALIS EXTRACT、MENTHOL、 MENTHONE GLYCERIN ACETAL、ARGININE、SUCRALOSE、PROPYLENE GLYCOL、 BUTYLENE GLYCOL、POLYSORBATE 20、CETYLPYRIDINIUM CHLORIDE、CITRIC ACID、 FLAVOR、SODIUM BENZOATE

INDICATIONS AND USAGE

It is recommended to use one(10ml) at a time, gargle for 30 seconds and spit out It's no need to garglewith water after use.

ACTIVE INGREDIENT

SODIUM FLUORIDE

DO NOT USE

Don't swallow it.

keep out of reach of children

PURPOSE

gargle

WARNINGS

Stopuse and aska doctor when feelinguncomfortable.